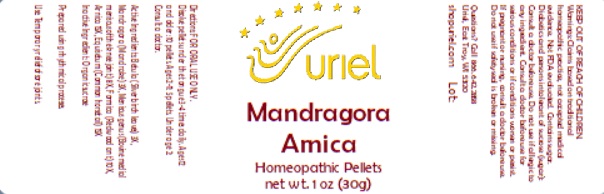 DRUG LABEL: Mandragora Arnica
NDC: 48951-8416 | Form: PELLET
Manufacturer: Uriel Pharmacy Inc.
Category: homeopathic | Type: HUMAN OTC DRUG LABEL
Date: 20241108

ACTIVE INGREDIENTS: BETULA PUBESCENS LEAF 3 [hp_X]/1 1; MANDRAGORA OFFICINARUM ROOT 3 [hp_X]/1 1; SUS SCROFA MENISCUS 6 [hp_X]/1 1; FORMICA RUFA 10 [hp_X]/1 1; ARNICA MONTANA 15 [hp_X]/1 1; EQUISETUM ARVENSE TOP 15 [hp_X]/1 1
INACTIVE INGREDIENTS: SUCROSE

Mandragora Arnica

INDICATIONS AND USAGE

Directions: FOR ORAL USE ONLY.

DOSAGE AND ADMINISTRATION

Dissolve pellets under the tongue 3-4 times daily. Ages 12 and older: 10 pellets. Ages 2-11: 5 pellets. Under age 2: Consult a doctor.

ACTIVE INGREDIENT

Active Ingredients: Betula (Silver birch leaves) 3X, Mandragora (Mandrake) 3X, Meniscus genus (Bovine medial meniscus of the knee joint) 8X, Formica (Redwood ant) 10X, Arnica 15X, Equisetum (Common horsetail) 15X

Inactive Ingredient: Organic sucrose

Prepared using rhythmical processes

PURPOSE

Use: Temporary relief of sore joints.

KEEP OUT OF REACH OF CHILDREN.

WARNINGS

Warnings: Claims based on traditional homeopathic practice, not accepted medical evidence. Not FDA evaluated. Contains sugar. Diabetics and persons intolerant of sucrose (sugar): Consult a doctor before use. Do not use if allergic to any ingredient. Consult a doctor before use for serious conditions or if conditions worsen or persist. If pregnant or nursing, consult a doctor before use. Do not use if safety seal is broken or missing.

QUESTIONS

Questions? Call 866.642.2858 Uriel, East Troy, WI 53120 shopuriel.com Lot: